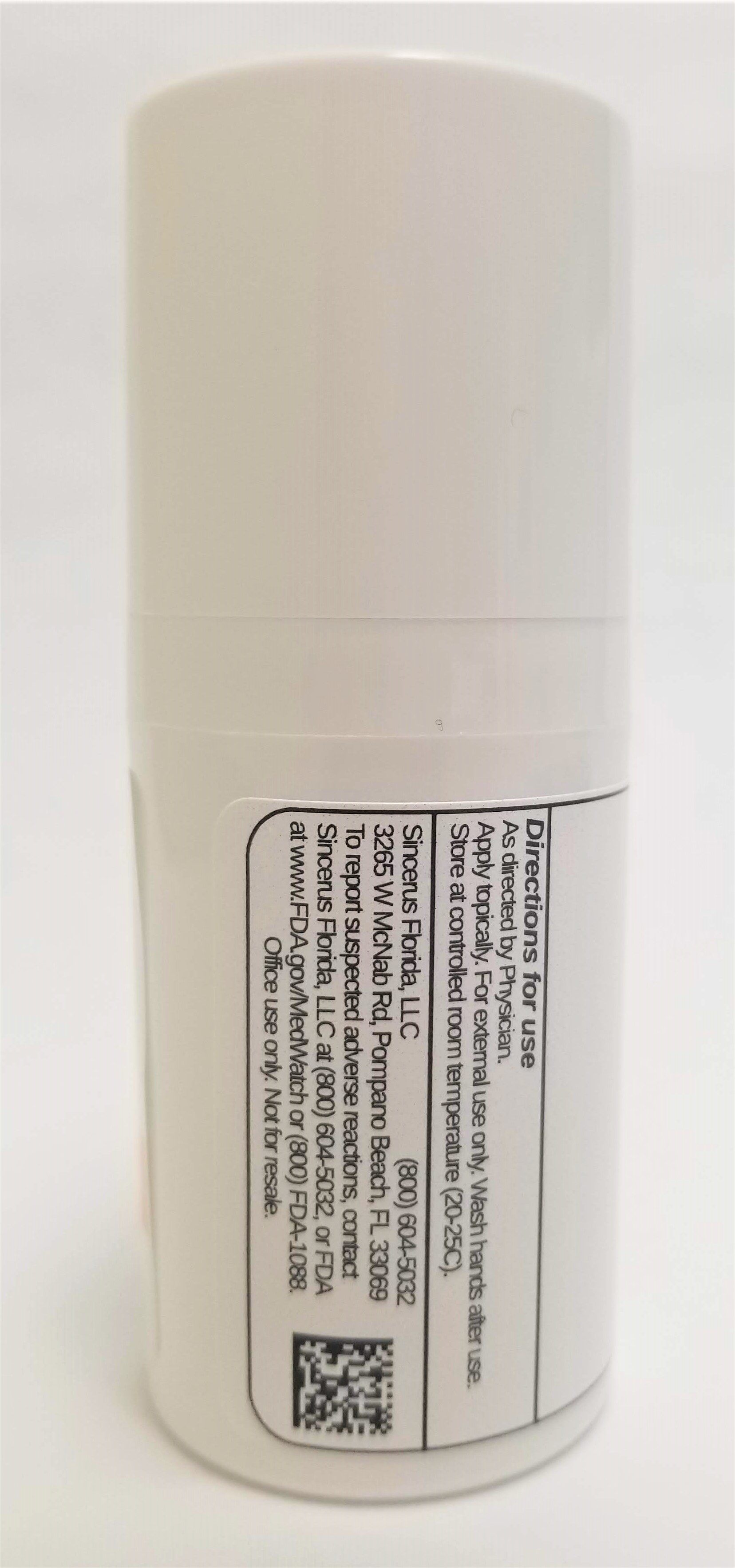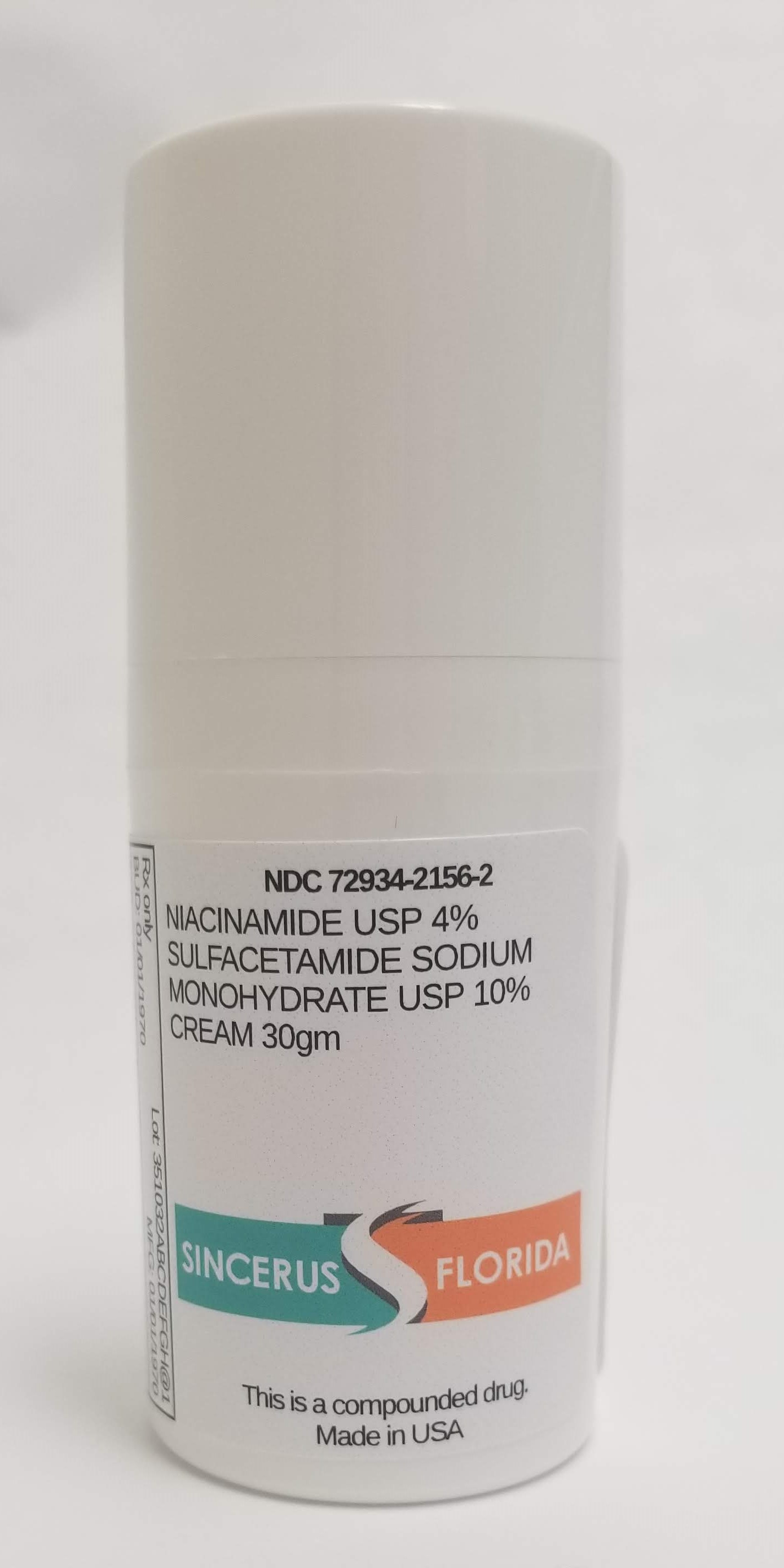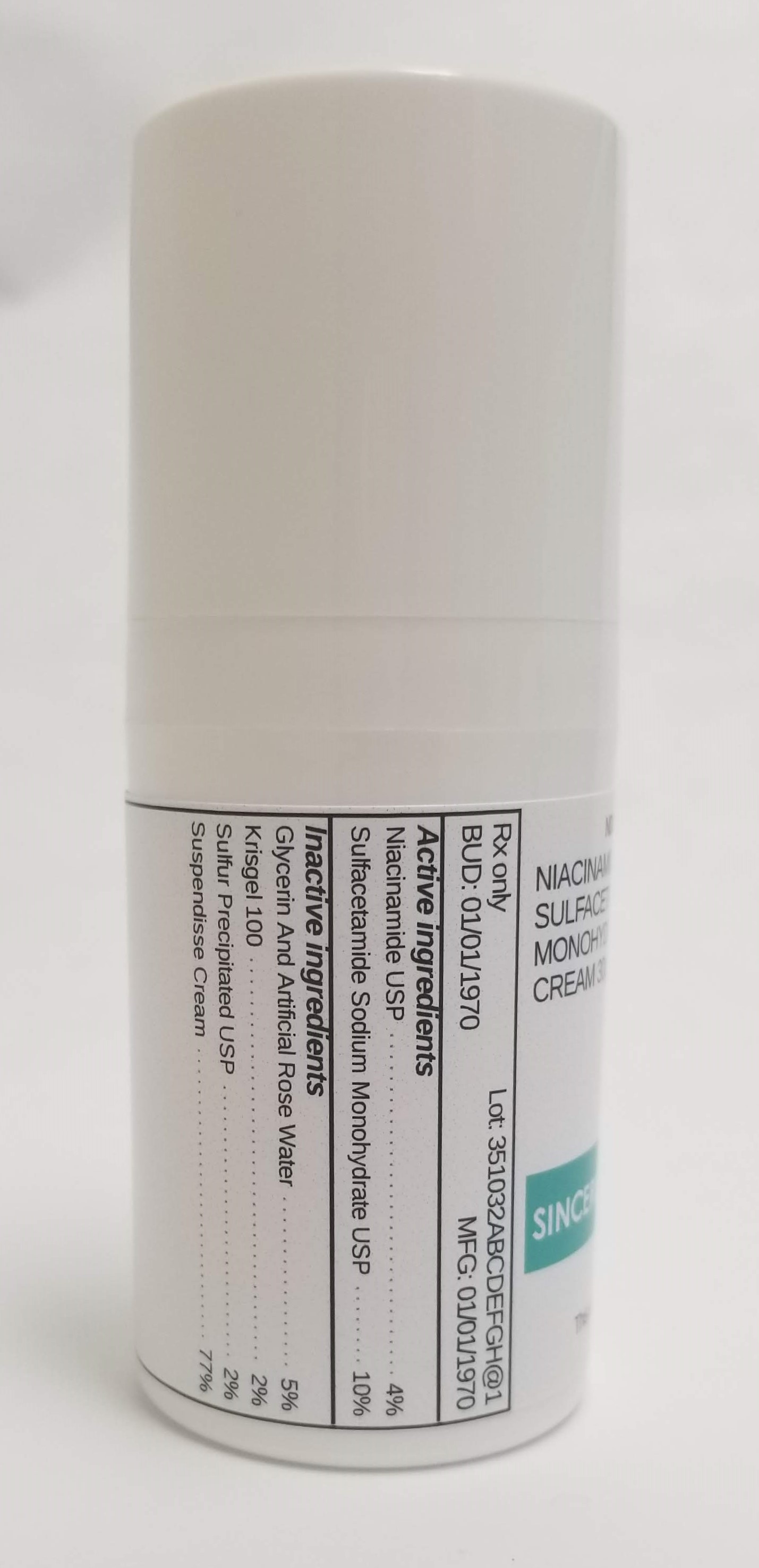 DRUG LABEL: NIACINAMIDE 4% / SODIUM SULFACETAMIDE MONOHYDRATE 10%
NDC: 72934-2156 | Form: CREAM
Manufacturer: Sincerus Florida, LLC
Category: prescription | Type: HUMAN PRESCRIPTION DRUG LABEL
Date: 20190522

ACTIVE INGREDIENTS: SULFACETAMIDE SODIUM 10 g/100 g; NIACINAMIDE 4 g/100 g

NIACINAMIDE 4% / SODIUM SULFACETAMIDE MONOHYDRATE 10%